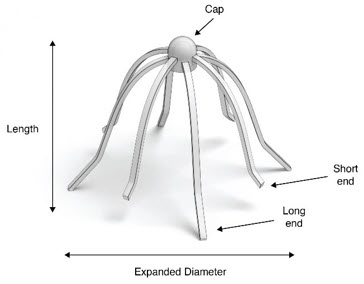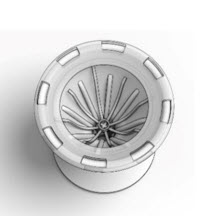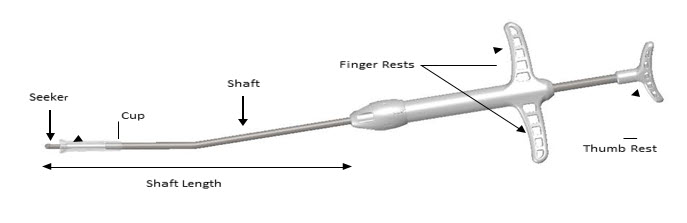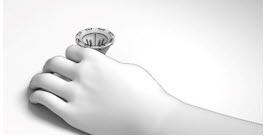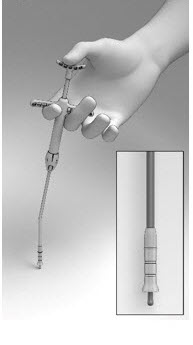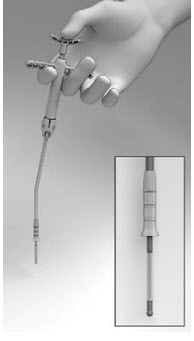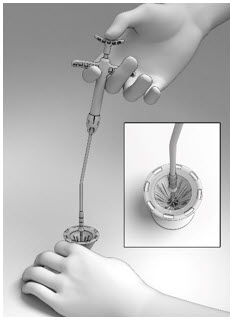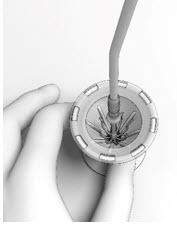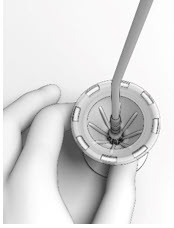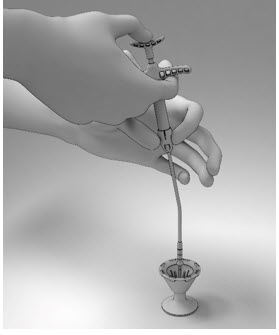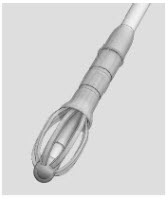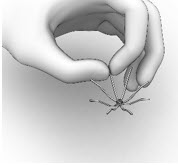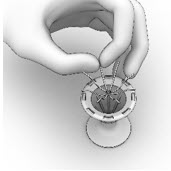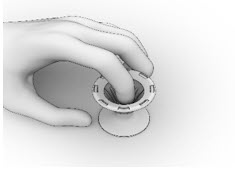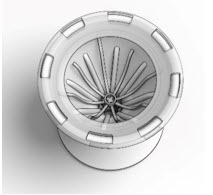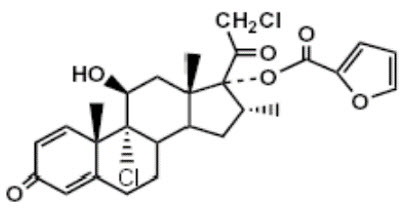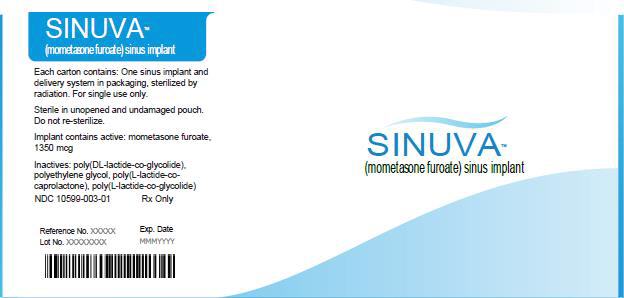 DRUG LABEL: Sinuva
NDC: 10599-003 | Form: IMPLANT
Manufacturer: Intersect ENT, Inc.
Category: prescription | Type: HUMAN PRESCRIPTION DRUG LABEL
Date: 20230126

ACTIVE INGREDIENTS: MOMETASONE FUROATE 1350 ug/1 1

HIGHLIGHTS OF PRESCRIBING INFORMATION

These highlights do not include all the information needed to use SINUVA® safely and effectively. See full prescribing information for SINUVA.
SINUVA (mometasone furoate) sinus implant
Initial U.S. Approval: 1987

1 INDICATIONS AND USAGE

SINUVA Sinus Implant is a corticosteroid-eluting implant indicated for the treatment of chronic rhinosinusitis with nasal polyps in adult patients ≥ 18years of age who have had ethmoid sinus surgery. (1)

2 DOSAGE AND ADMINISTRATION

- The SINUVA Sinus Implant is loaded into a Delivery System and placed in the ethmoid sinus under endoscopic visualization. The Implant may be left in the sinus to gradually release the corticosteroid over 90 days. Remove the implant by 90 days or earlier at the physician's discretion using standard surgical instruments. (2.2)
- To be inserted by physicians trained in otolaryngology. (2.3)

3 DOSAGE FORM AND STRENGTHS

Implant: 1350 mcg of mometasone furoate and a sterile Delivery System. (3)

4 CONTRAINDICATIONS

Patients with known hypersensitivity to mometasone furoate and any of the ingredients of the SINUVA Sinus Implant. (4)

5 WARNINGS AND PRECAUTIONS

- Monitor nasal mucosa adjacent to the SINUVA Sinus Implant for any signs of bleeding (epistaxis), irritation, infection, or perforation. Avoid use in patients with nasal ulcers or trauma. (5.1)
- Monitor patients with a change in vision or with a history of increased intraocular pressure, glaucoma, and/or cataracts closely. (5.2)
- Hypersensitivity reactions, including rash, pruritus, and angioedema, have been reported with use of corticosteroids. (5.3)
- Potential worsening of existing tuberculosis; fungal, bacterial, viral, or parasitic infection; or ocular herpes simplex. More serious or even fatal course of chickenpox or measles in susceptible patients. Use caution in patients with the above because of the potential for worsening of these infections. (5.4)
- If corticosteroid effects such as hypercorticism and adrenal suppression appear in patients, consider sinus implant removal. (5.5)

6 ADVERSE REACTIONS

The most common adverse reactions (in more than 1% of subjects) were bronchitis, nasopharyngitis, otitis media, headache, presyncope, asthma, and epistaxis. (6)

To report SUSPECTED ADVERSE REACTIONS, contact Intersect ENT at 1-866 531-6004 or FDA at 1-800-FDA-1088 or www.fda.gov/medwatch

FULL PRESCRIBING INFORMATION

1 INDICATIONS AND USAGE

SINUVA Sinus Implant is indicated for the treatment of chronic rhinosinusitis with nasal polyps in adult patients ≥18 years of age who have had ethmoid sinus surgery.

2 DOSAGE AND ADMINISTRATION

2.1 Recommended Dosage

The recommended dosage is one SINUVA Sinus Implant (1350 mcg of mometasone furoate) placed in an ethmoid sinus [see Dosage and Administration (2.3)]. The SINUVA Sinus Implant may be left in the sinus to gradually release the corticosteroid over 90 days. Remove the SINUVA Sinus Implant by 90 days or earlier at the physician's discretion [see Dosage and Administration (2.4)].

2.2 Health Care Provider Training

The SINUVA Sinus Implant is to be used by physicians trained in otolaryngology. Specialized training is not required for these physicians.

2.3 Placement of SINUVA Sinus Implant

The SINUVA Sinus Implant is designed for single patient use only. Do not reprocess or reuse.

- Do not use if the package is open, the package or product is damaged, or has evidence of gross contamination.
- Special care should be taken to avoid bending, twisting, or damaging the implant.
- The implant is not designed to be modified by the physician.
- The implant is not intended to be compressed and loaded into the Delivery System more than two times. The implant must be placed under endoscopic visualization.

Patient Preparation

The patient should be prepared following routine protocols for in-office sinonasal endoscopic procedures.

Implant Preparation

The SINUVA Sinus Implant (Figure 1) is loaded into a Delivery System and placed in the ethmoid sinus.

Remove the Crimper (Figure 2) and the Delivery System (Figure 3) from their protective packaging using sterile technique. Inspect the SINUVA Sinus Implant located inside of the Crimper (Figure 2). Do not remove the Implant from the Crimper. Prior to use, the SINUVA Sinus Implant must be crimped and loaded into the Delivery System.

If the SINUVA Sinus Implant is not fully seated inside of the Crimper, secure the SINUVA Sinus Implant before proceeding. See instructions to secure the SINUVA Sinus Implant (Figure 12–15).

IMPLANT | Length (nominal): | 20 mm
IMPLANT | Expanded Diameter (nominal): | 34 mm
DELIVERY SYSTEM | Shaft Length | 117 mm

Figure 1: Implant

Figure 2: Crimper with Implant

Figure 3: Delivery System

1. Place the Crimper on a flat surface and hold to prevent any potential slipping of the Crimper during loading of the SINUVA Sinus Implant into the Delivery System. Orient the Crimper such that the short ends of the Implant are in the 12 o'clock and 6 o'clock position (Figure 4).
  Figure 4
2. Grasp the Delivery System with the index and middle fingers on the left or right hand using the Finger Rests and the thumb in the Thumb Rest (Figure 5).
  Figure 5
3. Pull back on the Finger Rests while pressing down on the Thumb Rest to retract the Cup and expose the Seeker (Figure 6).
  Figure 6
4. Position the tip of the Seeker with its 10° angled tip downwards toward the user in the depression in the center of the SINUVA Sinus Implant (Figure 7). The distal end of the angled shaft must be in a vertical position, perpendicular to the Crimper, during positioning. Ensure the plane of the angled tip is in the same plane as the short ends of the Implant that were oriented in the 12 o'clock / 6 o'clock position in step 1.
  Figure 7
5. With the Thumb Rest depressed, gradually apply perpendicular downward force to the SINUVA Sinus Implant until the ends of the Implant collapse around the Seeker of Delivery System (Figure 8). Make sure that the Finger Rests are not released while pushing downwards.
  Figure 8
6. The SINUVA Sinus Implant should crimp in a radial fashion onto the Seeker. Implant ends should not cross over or past each other when being crimped onto the Seeker by the Crimper.
7. While maintaining steady downward pressure on the Thumb Rest, slowly release the Finger Rests with the index and middle fingers until the Cup lowers and captures all ends of the SINUVA Sinus Implant (Figure 9). If necessary, adjust the position of the Delivery System with slight circular movements, slightly lifting and then lowering the Cup into position to ensure that all eight ends of the SINUVA Sinus Implant are secured within the Cup.
  Figure 9
8. Apply a downward push on the Delivery System to ensure that the SINUVA Sinus Implant is secured in the Cup (Figure 10). This will also ensure the Implant is compressed to its smallest profile for insertion.
  Figure 10
9. Retract the Delivery System from the Crimper. The SINUVA Sinus Implant should remain symmetrically loaded in the Cup of the Delivery System (Figure 11).
  Figure 11

CAUTION: Do not leave the SINUVA Sinus Implant in the crimped state for more than 5 minutes prior to placement.

Instructions to Secure the SINUVA Sinus Implant in the Crimper

If necessary, the Implant may be reloaded into the Crimper for a second time.

CAUTION: The SINUVA Sinus Implant should not be used if the second attempt to crimp is unsuccessful.

1. Hold the SINUVA Sinus Implant by one end as shown in Figure 12.
  Figure 12
2. Holding the SINUVA Sinus Implant with the dome-shaped Cap positioned downward (Figure 13), place the Implant back into the Crimper.
  Figure 13
3. Ensure that each Implant is secured in the Crimper by pressing down on the center of the Implant until all ends of the Implant are below the rim of the Crimper (Figure 14).
  Figure 14
4. Inspect the Implant and the Crimper to ensure that all the Implant ends are secured below the rim of the Crimper (Figure 15). Return to Implant Preparation Step 1 for instructions on how to load the re-secured implant into the delivery system.
  Figure 15

Instructions for the SINUVA Sinus Implant Placement

Advance the Delivery System under endoscopic visualization into the ethmoid sinus cavity.

1. Ensure that the Delivery System is oriented such that the 10° curvature of the distal tip is curved superiorly. Insert the Delivery System such that the Shaft is parallel to roof of ethmoid sinus.
2. If the SINUVA Sinus Implant becomes dislodged from the Delivery System prior to placement into the ethmoid sinus, remove the Implant and inspect for damage, re-load the undamaged Implant in the Crimper, and re-crimp the Implant into the Delivery System. Note that the SINUVA Sinus Implant should not be loaded into the Delivery System more than twice.
3. Release the SINUVA Sinus Implant by pressing down on the Thumb Rest while pulling back on the Finger Rests in a controlled manner.
4. Place the SINUVA Sinus Implant amongst the sinus polyps with the cap oriented toward the posterior ethmoid sinus, and with the Implant positioned as superiorly as possible in the sinus. The long ends of the Implant should be in approximately the 2 o'clock, 4 o'clock, 8 o'clock and 10 o'clock positions, respectively. Confirm final placement of the SINUVA Sinus Implant by endoscopic visualization. To adjust the position of the SINUVA Sinus Implant, use the Seeker on the Delivery System or standard endoscopic surgical instruments.

Post Placement Instructions

Reposition the Implant if its ends are perpendicular to and in contact with the nasal septum. Avoid excessive manipulation of the Implant during follow-up, as this can cause dislodgement.

2.4 Removal Instructions

The SINUVA Sinus Implant is made from bioabsorbable polymers designed to gradually soften over time. Remove the SINUVA Sinus Implant by day 90 or earlier at the physician's discretion using standard endoscopic instruments.

3 DOSAGE FORM AND STRENGTHS

Implant: a sterile, single-use, bioabsorbable implant, coated with a formulation containing 1350 mcg mometasone furoate that is gradually released over 90 days.

4 CONTRAINDICATIONS

Patients with known hypersensitivity to mometasone furoate, or to any of the copolymers of the SINUVA Sinus Implant [see Description (11)].

5 WARNINGS AND PRECAUTIONS

5.1 Local Nasal Adverse Reactions

Monitor nasal mucosa adjacent to the SINUVA Sinus Implant for any signs of bleeding (epistaxis), irritation, infection, or perforation. Avoid use in patients with nasal ulcers or trauma.

5.2 Glaucoma and Cataracts

Nasal steroids may result in development of glaucoma and/or cataracts. Glaucoma, cataracts, and clinically significant elevation of intraocular pressure were not observed in patients from the treatment group of one randomized controlled clinical study (N = 53) who underwent bilateral placement of SINUVA Sinus Implants. Close monitoring is warranted in patients with a change in vision or with a history of increased intraocular pressure, glaucoma, and/or cataracts.

5.3 Hypersensitivity Reactions

Hypersensitivity reactions, including rash, pruritus, and angioedema have been reported with use of corticosteroids.

5.4 Immunosuppression and Risk of Infections

Persons who are using drugs that suppress the immune system, such as corticosteroids, including SINUVA Sinus Implant are more susceptible to infections than healthy individuals. Chickenpox and measles, for example, can have a more serious or even fatal course in susceptible children or adults using corticosteroids. In such children or adults who have not had these diseases or who are not properly immunized, particular care should be taken to avoid exposure. How the dose, route, and duration of corticosteroid administration affect the risk of developing a disseminated infection is not known. The safety and effectiveness of SINUVA Sinus Implant have not been established in pediatric patients less than 18 years of age and SINVA is not indicated for use in this population.

The contribution of the underlying disease and/or prior corticosteroid treatment to the risk is also not known. If exposed to chickenpox, prophylaxis with varicella zoster immune globulin (VZIG) may be indicated. If exposed to measles, prophylaxis with pooled intramuscular immunoglobulin (IG) may be indicated (See the respective Prescribing Information for VZIG and IG). If chickenpox develops, treatment with antiviral agents may be considered.

Corticosteroids should be used with caution, if at all, in patients with active or quiescent tuberculosis infection of the respiratory tract; untreated systemic fungal, bacterial, viral, or parasitic infections; or ocular herpes simplex.

5.5 Hypercorticism and Adrenal Suppression

Hypercorticism and adrenal suppression were not evaluated as part of the SINUVA Sinus Implant clinical program.

Since individual sensitivity to effects of cortisol production exists, physicians should consider this information when prescribing SINUVA Sinus Implant. Particular care should be taken in observing patients postoperatively or during periods of stress for evidence of inadequate adrenal response.

It is possible that systemic corticosteroid effects such as hypercorticism and adrenal suppression may appear in patients, particularly when systemic mometasone furoate is administered at higher than recommended doses over prolonged periods of time. If such effects occur, consider sinus implant removal.

6 ADVERSE REACTIONS

The following clinically significant adverse reactions are described elsewhere in the labeling:

- Local Nasal Adverse Reactions [see Warnings and Precautions (5.1)]
- Glaucoma and Cataracts [see Warnings and Precautions (5.2)]
- Hypersensitivity Reactions [see Warnings and Precautions (5.3)]
- Immunosuppression and Risk of Infections [see Warnings and Precautions (5.4)]
- Hypercorticism and Adrenal Suppression [see Warnings and Precautions (5.5)]

6.1 Clinical Trials Experience

Because clinical trials are conducted under widely varying conditions, adverse reaction rates observed in the clinical trials of a drug cannot be directly compared to rates in the clinical trials of another drug and may not reflect the rates observed in practice.

The safety of the SINUVA Sinus Implant was evaluated and demonstrated in 400 patients in 2 controlled, randomized, parallel group, single-blind studies. In Study 1, one-hundred (100) subjects were followed for 6 months. In Study 2, three-hundred (300) subjects were followed for 90 days. Of the 400 patients, 254 were assigned to the treatment group and underwent bilateral placement of SINUVA Sinus Implants in the ethmoid sinuses, totaling 2700 mcg of mometasone furoate, and 146 patients were assigned to the control group and underwent a sham procedure consisting of advancement of the Delivery System with the SINUVA Sinus Implant followed by removal without deployment. The Implants were removed by Day 60. All patients were required to use mometasone furoate nasal spray once daily (200 mcg of mometasone furoate) through Day 90.

Table 1 shows the common adverse reactions (in greater than 1% of subjects) that occurred more frequently in patients treated with SINUVA Sinus Implant compared to the control group.

Table 1: Adverse Reactions with > 1% Incidence and More Common than Control in 90-Day Controlled Clinical Trials with SINUVA Sinus Implant
 | Study 1 & Study 2 Combined Data
Adverse Reaction | Treatment [Patients in the treatment group received SINUVA Sinus Implants placed bilaterally in the ethmoid sinuses and used mometasone furoate nasal spray once daily (200 mcg mometasone furoate) through Day 90.] (N = 254) n (%) | Control [Patients in the control group underwent a sham procedure and used mometasone furoate nasal spray once daily (200 mcg mometasone furoate) through Day 90.] (N = 146) n (%)
Asthma | 12 (4.7) | 6 (4.1)
Headache | 9 (3.5) | 5 (3.4)
Epistaxis | 6 (2.4) | 2 (1.4)
Presyncope | 6 (2.4) | 3 (2.1)
Bronchitis | 5 (2.0) | 2 (1.4)
Otitis media | 5 (2.0) | 2 (1.4)
Nasopharyngitis | 3 (1.2) | 1 (0.7)
Values represent patient counts and percentages. A patient reporting more than one adverse event for a particular MedDRA preferred term is counted only once.

Study 1 monitored patients from Day 90 through 6 months. Hypersensitivity (4% (n=2) vs. 0), chronic rhinosinusitis (11% (n=6) vs. 9% (n=4)), and upper respiratory tract infections (8% (n=4) vs. 2% (n=1)) were reported in more than 2 subjects in the treatment group, and more commonly than the control group during this time period.

The safety of repeat administration of the SINUVA Sinus Implant was evaluated in Study 3 that was an open-label, single-arm, multicenter study in 50 patients. All patients underwent an in- office bilateral placement of the SINUVA Sinus Implant in each ethmoid sinus (totaling 2 implants) and were followed for 365 days. Patients were required to use mometasone furoate nasal spray once daily (200 mcg of mometasone furoate) through 365 days. At 90 days, the remaining implants were removed. To maximize the size of the safety population, patients with ethmoid sinus polyps grade ≥ 1 on any side were considered for repeat implant placement. Repeat placement was not performed if polyp grade was < 1, or if the patient declined it. Of the 50 patients, 41 received repeat implant placement (33 bilaterally and 8 unilaterally). Acute sinusitis (29%, n=12), upper respiratory infection (17%, n=7) epistaxis (12%, n=5), nasal discomfort or rhinalgia (12%, n=5), headache (7%, n=3), were the common adverse reactions that occurred in at least 3 subjects who underwent repeat placement during the study period.

6.2 Postmarketing Experience

The following adverse reactions have been identified during postapproval use of the SINUVA sinus implant. These events have been chosen for inclusion due to either their seriousness, frequency of reporting, possible causal connection to SINUVA, or a combination of these factors, include: implant migration, lack of efficacy, nasal pain, headache, epistaxis. Because these reactions are reported voluntarily from a population of uncertain size, it is not always possible to reliably estimate their frequency or establish a causal relationship to drug experience.

7 DRUG INTERACTIONS

Formal drug-drug interaction studies have not been conducted with the SINUVA Sinus Implant. An evaluation of the concurrent administration of the SINUVA Sinus Implant and other commonly used nasal drugs was not associated with any unusual adverse reactions.

7.1 Inhibitors of Cytochrome P450 3A4

Co-administration with ketoconazole, a potent CYP 3A4 inhibitor, may increase the plasma concentrations of mometasone furoate [see Clinical Pharmacology (12.3)].

8 USE IN SPECIFIC POPULATIONS

8.1 Pregnancy

Risk Summary

There are no randomized clinical studies of SINUVA Sinus Implant or mometasone furoate in pregnant women. The active pharmaceutical ingredient, mometasone furoate is systemically available when administered topically or when inhaled. In animal reproduction studies, subcutaneous administration of mometasone furoate to pregnant mice, rats, or rabbits caused increased fetal malformations and decreased fetal survival and growth following administration of doses that produced exposures approximately 1/3 to 8 times the maximum recommended human dose (MRHD) on a mcg/m^2 or AUC basis (see Data). However, experience with oral corticosteroids suggests that rodents are more prone to teratogenic effects from corticosteroid exposure than humans.

The estimated background risk of major birth defects and miscarriage for the indicated population is unknown. In the U.S. general population, the estimated risk of major birth defects and miscarriage in clinically recognized pregnancies is 2% to 4% and 15% to 20%, respectively.

Data

Animal Data

In an embryofetal development study with pregnant mice dosed throughout the period of organogenesis, mometasone furoate produced cleft palate at an exposure approximately one-third of the MRHD (on a mcg/m^2 basis with maternal subcutaneous doses of 60 mcg/kg and above) and decreased fetal survival at an exposure approximately equivalent to the MRHD (on a mcg/m^2 basis with a maternal subcutaneous dose of 180 mcg/kg). No toxicity was observed with a dose that produced an exposure approximately one-tenth of the MRHD (on a mcg/m^2 basis with maternal topical dermal doses of 20 mcg/kg and above).

In an embryofetal development study with pregnant rats dosed throughout the period of organogenesis, mometasone furoate produced fetal umbilical hernia at exposures approximately 6 times the MRHD (on a mcg/m2 basis with maternal topical dermal doses of 600 mcg/kg and above) and delays in fetal ossification at exposures approximately 3 times the MRHD (on a mcg/m2 basis with maternal topical dermal doses of 300 mcg/kg and above).

In another reproductive toxicity study, pregnant rats were dosed with mometasone furoate throughout pregnancy or late in gestation. Treated animals had prolonged and difficult labor, fewer live births, lower birth weight, and reduced early pup survival at an exposure that was approximately 8 times the MRHD (on an area under the curve (AUC) basis with a maternal subcutaneous dose of 15 mcg/kg). There were no findings with an exposure approximately 4 times the MRHD (on an AUC basis with a maternal subcutaneous dose of 7.5 mcg/kg).

Embryofetal development studies were conducted with pregnant rabbits dosed with mometasone furoate by either the topical dermal route or oral route throughout the period of organogenesis. In the study using the topical dermal route, mometasone furoate caused multiple malformations in fetuses (e.g., flexed front paws, gallbladder agenesis, umbilical hernia, hydrocephaly) at an exposure approximately 3 times the MRHD (on a mcg/m^2 basis with maternal topical dermal doses of 150 mcg/kg and above). In the study using the oral route, mometasone furoate caused increased fetal resorptions and cleft palate and/or head malformations (hydrocephaly and domed head) at an exposure approximately 1/2 of the MRHD (on AUC basis with a maternal oral dose of 700 mcg/kg). At an exposure approximately 2 times the MRHD (on an AUC basis with a maternal oral dose of 2800 mcg/kg), most litters were aborted or resorbed. No effects were observed at an exposure approximately 1/10 of the MRHD (on an AUC basis with a maternal oral dose of 140 mcg/kg).

8.2 Lactation

Risk Summary

There are no available data on the presence of SINUVA Sinus Implant in human milk, the effects on the breastfed child or the effects on milk production. Systemic absorption of a single inhaled 400 mcg mometasone dose was less than 1%. It is not known if mometasone furoate is excreted in human milk. Other inhaled corticosteroids, similar to mometasone furoate, are present in human milk. The developmental and health benefits of breastfeeding should be considered along with the mother's clinical need for the SINUVA Sinus Implant and any potential adverse effects on the breastfed infant from the SINUVA Sinus Implant.

8.4 Pediatric Use

The safety and effectiveness of the SINUVA Sinus Implant have not been established in pediatric patients less than 18 years of age.

8.5 Geriatric Use

A total of 33 patients 65 years of age or older received the SINUVA Sinus Implant in 2 controlled randomized clinical trials. Clinical studies did not include sufficient numbers of subjects aged 65 and over to determine whether they respond differently from younger subjects.

8.6 Hepatic Impairment

Concentrations of mometasone furoate appear to increase with severity of hepatic impairment [see Clinical Pharmacology (12.3)].

10 OVERDOSAGE

There are no data available on the effects of acute or chronic overdosage with SINUVA Sinus Implant. Chronic overdosage may result in signs/symptoms of hypercorticism [see Warnings and Precautions (5.5)].

11 DESCRIPTION

The SINUVA Sinus Implant is a self-expanding, bioabsorbable, drug eluting implant provided with a crimper and a single-use delivery system. SINUVA Sinus Implant is comprised of poly(L-lactide-co-glycolide) and poly(L-lactide-co-⃞-caprolactone) coated with mometasone furoate embedded in a bioabsorbable polymer matrix containing poly(DL-lactide-co-glycolide) and polyethylene glycol (inactive ingredients) which provides for gradual release of the drug. The SINUVA Sinus Implant is packaged in a tray, which is then sealed in a foil pouch and placed in the product carton. The SINUVA Sinus Implant is provided sterile.

Mometasone furoate, the active component of the SINUVA Sinus Implant, is a corticosteroid with the chemical name 9,21-dichloro-11(⃞),17-dihydroxy-16(⃞)-methylpregna-1,4-diene-3,20- dione 17 (2-furoate). Mometasone furoate is a white powder with an empirical formula of C27H30Cl2O6, and molecular weight of 521.44 Daltons.

The chemical structure of mometasone furoate is shown below:

The inactive ingredients are poly-(DL-lactide-co-glycolide) and polyethylene glycol. Poly-(DL-lactide-co-glycolide) is an amorphous biodegradable polymer.

12 CLINICAL PHARMACOLOGY

12.1 Mechanism of Action

Mometasone furoate is a corticosteroid demonstrating potent anti-inflammatory activity. The precise mechanism of corticosteroid action on inflammation is not known. Corticosteroids have been shown to have a wide range of effects on multiple cell types (e.g., mast cells, eosinophils, neutrophils, macrophages, and lymphocytes) and mediators (e.g., histamine, eicosanoids, leukotrienes, and cytokines) involved in inflammation.

12.2 Pharmacodynamics

Adrenal Function

The effects of the SINUVA Sinus Implant on adrenal function have not been evaluated in clinical studies.

12.3 Pharmacokinetics

One pharmacokinetics study was conducted with the SINUVA Sinus Implant. The remaining information is from other products containing mometasone furoate.

Absorption

A pharmacokinetics study was conducted to evaluate the potential for systemic exposure to mometasone furoate from the sinonasal route of administration following bilateral placement of the SINUVA Sinus Implant. Baseline blood samples were taken before the procedure, and on Days 3, 7, 14, 21 and 30 to assess systemic concentrations of mometasone furoate in plasma. Six out of fifteen PK samples from five subjects had measurable mometasone furoate plasma concentrations from Day 3 to Day 14. All the measurable concentrations were within 2.5-fold of the lower limit of quantitation (LLOQ; 30 pg/mL). No PK samples had measurable mometasone furoate plasma concentrations after Day 14.

Distribution

Following an intravenous 400 mcg dose of mometasone furoate, the mean steady state volume of distribution was 152 L. The in vitro protein binding for mometasone furoate was reported to be 98% to 99% (in concentration range of 5 to 500 ng/mL).

Elimination

Metabolism

Studies have shown that mometasone furoate is primarily and extensively metabolized in the liver of all species investigated and undergoes extensive metabolism to multiple metabolites. In vitro studies have confirmed the primary role of CYP 3A4 in the metabolism of this compound; however, no major metabolites were identified.

Excretion

Following intravenous dosing, the terminal half-life was reported to be about 5 hours.

Specific Populations

The effects of renal impairment, hepatic impairment, age, or gender on mometasone furoate pharmacokinetics have not been adequately investigated.

Drug Interaction Studies

Formal drug-drug interaction studies have not been conducted with the SINUVA Sinus Implant.

13 NONCLINICAL TOXICOLOGY

13.1 Carcinogenesis, Mutagenesis, Impairment of Fertility

In a 2-year carcinogenicity study in Sprague Dawley rats, mometasone furoate demonstrated no statistically significant increase of tumors at inhalation doses up to 67 mcg/kg (approximately 14 times the MRHD on an AUC basis). In a 19-month carcinogenicity study in Swiss CD-1 mice, mometasone furoate demonstrated no statistically significant increase in the incidence of tumors at inhalation doses up to 160 mcg/kg (approximately 9 times the MRHD on an AUC basis).

Mometasone furoate increased chromosomal aberrations in an in vitro Chinese hamster ovary cell assay, but did not have this effect in an in vitro Chinese hamster lung cell assay. Mometasone furoate was not mutagenic in the Ames test or mouse lymphoma assay, and was not clastogenic in an in vivo mouse micronucleus assay, a rat bone marrow chromosomal aberration assay, or a mouse male germ-cell chromosomal aberration assay. Mometasone furoate also did not induce unscheduled DNA synthesis in vivo in rat hepatocytes.

In reproductive studies in rats, impairment of fertility was not produced by subcutaneous doses up to 15 mcg/kg (approximately 8 times the MRHD on an AUC basis).

14 CLINICAL STUDIES

The SINUVA Sinus Implant was evaluated in 450 patients, 18 years of age and older, with chronic rhinosinusitis with nasal polyps and a history of ethmoid sinus surgery. The development program included a trial of 6 months duration (Study 1: NCT01732536), another trial of 90 days duration (Study 2: NCT02291549), and a repeat placement study of 1-year duration (Study 3: NCT03358329) [see Adverse Reactions (6.1)]. The efficacy of SINUVA Sinus Implant is based primarily on Study 2 as described below.

Study 2 was a randomized, controlled, single-blind, multicenter (all sites were in the US) study with 300 patients: 201 patients were assigned to the treatment group and underwent bilateral placement of the SINUVA Sinus Implants in the ethmoid sinuses. The remaining 99 patients were assigned to the control group and underwent a placebo (sham) procedure, consisting of advancement of the Delivery System with the SINUVA Sinus Implant into the ethmoid sinuses, followed by removal of the Delivery System without deployment of the SINUVA Sinus Implant. The Implants were removed by Day 60 to allow blinded grading at Day 90. All patients [treatment (T) and control (C) groups] were required to use a mometasone furoate nasal spray once daily (200 mcg of mometasone furoate) through Day 90.

The co-primary efficacy endpoints were:

- Change from baseline to Day 30 in Nasal Obstruction/Congestion score, as determined by patients using a daily diary; and
- Change from baseline to Day 90 in bilateral polyp grade, as determined from video- endoscopies reviewed by an independent panel of 3 sinus surgeons who were masked to treatment assignment.

The study population consisted of adult patients (≥ 18 years of age) diagnosed with chronic rhinosinusitis who had undergone prior bilateral total ethmoidectomy but were indicated for revision endoscopic sinus surgery because they presented with recurrent nasal obstruction/congestion symptoms and recurrent bilateral sinus obstruction due to nasal polyps. Subjects were excluded for other grade 3 or 4 adhesions/synechiae, grade 4 polyps, acute bacterial or invasive fungal sinusitis, and immune deficiency, including cystic fibrosis. There were no statistically significant differences between groups in baseline demographics and clinical characteristics, except the treatment group had a higher proportion of asthma patients (T: 74% vs. C: 62%) and higher mean Percent Ethmoid Sinus Obstruction score [T: 76 (SD 17.4) vs. C: 69 (SD 19.9)]. The random imbalances did not impact treatment effect.

The co-primary efficacy results are presented in Table 2. The treatment group demonstrated a statistically significant difference from baseline to Day 30 in Nasal Obstruction/Congestion score and from baseline to Day 90 in bilateral polyp grade, compared to the control group.

Table 2: Co-Primary Efficacy Results with the SINUVA Sinus Implant (Study 2)
 |  | Treatment (N = 201) | Control (N = 99)
Nasal Obstruction/Congestion Score [Change from baseline in Nasal Obstruction/Congestion was assessed on a scale of 0–3 where 0=no symptoms, 1=mild symptoms, 2=moderate symptoms, and 3=severe symptoms. Scores were assessed using a daily diary for 7 days immediately preceding the baseline and Day 30 visits.]
N |  | 201 | 99
Baseline, Mean (SD) |  | 2.36 (0.49) | 2.35 (0.48)
Change from Baseline, Mean (SD) |  | -0.80 (0.73) | -0.56 (0.62)
Difference vs. Control (95% CI) [Based on analysis of covariance (ANCOVA) model with baseline value as a covariate and site and treatment group as fixed effects.] |  | -0.23 (-0.39, -0.06)
Bilateral Polyp Grade [c) Change from baseline to Day 90 in bilateral polyp grade was assessed based on grading of video-endoscopies by an independent panel of 3 sinus surgeons who were blinded to treatment assignment. Polyps were graded as follows: 0=no visible polyps, 1=Small amount of polyps confined in middle meatus, 1.5= 1+ polypoid edema obstructing ≥ 25% of the ethmoid sinus cavity, 2=Expanded amount of polyps confined in middle meatus, 2.5 = 2 + polypoid edema obstructing ≥ 50% of the ethmoid sinus cavity, 3= Polyps extending beyond middle meatus, but not totally obstructing the nasal cavity, 3.5= 3 + polypoid edema obstructing ≥ 75% of the ethmoid sinus cavity, 4= Polyps completely obstructing the nasal cavity.]
N |  | 195 | 97
Baseline, Mean (SD) |  | 5.48 (1.13) | 5.43 (1.01)
Change from Baseline, Mean (SD) |  | -0.56 (1.06) | -0.15 (0.91)
Difference vs. Control (95% CI) |  | -0.35 (-0.60, -0.09)

Change from baseline to Day 90 in the mean Percent Ethmoid Sinus Obstruction score (100 mm VAS), as judged by the independent panel [Difference vs. control: -7.96%; 95% CI (-12.1, -3.8)], met statistical significance and supported the co-primary endpoints.

16 HOW SUPPLIED/STORAGE AND HANDLING

A carton of SINUVA contains one SINUVA (1350 mcg mometasone furoate) implant inside of a Crimper and one disposable Delivery System packaged in a foil pouch. The SINUVA Sinus Implant is 20 mm in length and 34 mm in expanded diameter (Figure 1).

STORAGE AND HANDLING

Store the SINUVA Sinus Implant at 20° C– 25°C (68°F–77°F); excursions permitted at 15°C –30°C (59°F– 86°F) [see USP Controlled Room Temperature].

The NDC code for the SINUVA Sinus Implant is 10599-003-01.

17 PATIENT COUNSELING INFORMATION

- Encourage patients to use saline irrigations or sprays regularly.
- Advise the patient that the Implant is bioabsorbable and intended to soften over time. As the Implant softens and polyps decrease, the Implant may be expelled out of the nose on its own or with actions such as sneezing or forceful nose blowing.
- Advise the patient to call a health care professional immediately if they experience any of the following:
  - Excessive nasal bleeding or symptoms of infection, such as excessive pain or discomfort, persistent headache, increased sinus discharge.
  - Symptoms suggesting the Implant has migrated posteriorly, such as irritation or choking sensation in the back of the throat or swallowing the Implant.

Risks Relating to the Insertion and Removal Procedure

Inform patients that there are risks associated with the insertion and removal of the SINUVA Sinus Implant. These risks are similar to those associated with other endoscopic sinus procedures.

Local Nasal Adverse Reactions

Patients should be informed that treatment with the SINUVA Sinus Implant may be associated with local adverse reactions such as nose-bleed (epistaxis), injury to nerves or blood vessels of the middle turbinate or septum, bacterial or candida infection. Because of the potential inhibitory effect of corticosteroids on wound healing, patients who have experienced recent nasal septum ulcers, nasal surgery, or nasal trauma should not use a nasal corticosteroid until healing has occurred [see Warnings and Precautions (5.1) and Adverse Reactions (6)].

Hypersensitivity Reactions

Hypersensitivity reactions, including rash, pruritus, and angioedema, have been reported with use of mometasone furoate. Remove the SINUVA Sinus Implant if such reactions occur [see Contraindications (4), Warnings and Precautions (5.3), and Adverse Reactions (6)].

Immunosuppression and Risk of Infections

Patients who are on immunosuppressant doses of corticosteroids should be warned to avoid exposure to chickenpox or measles and, if exposed, to consult their physician without delay. Patients should be informed of potential worsening of existing tuberculosis; fungal, bacterial, viral, or parasitic infections; or ocular herpes simplex [see Warnings and Precautions (5.4)].

This product and/or the use of this product in a method may be covered by one or more patents or patent applications, available at www.sinuva.com

© 2020 Intersect ENT, Inc. All rights reserved. INTERSECT ENT and SINUVA are trademarks or registered trademarks of Intersect ENT, Inc.

Manufactured by:
Intersect ENT
1555 Adams Dr.
Menlo Park, CA 94025

PRINCIPAL DISPLAY PANEL - 1350 mcg Implant Pouch Carton

SINUVA™
(mometasone furoate) sinus implant